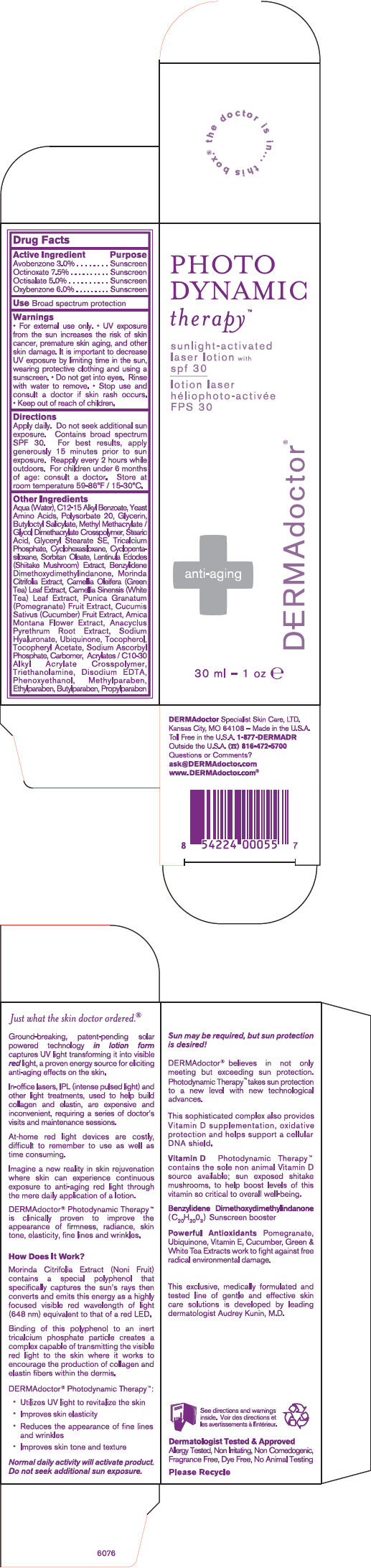 DRUG LABEL: PHOTO DYNAMIC THERAPY SPF 30
NDC: 65113-2432 | Form: LOTION
Manufacturer: G.S. COSMECEUTICAL USA, INC.
Category: otc | Type: HUMAN OTC DRUG LABEL
Date: 20101109

ACTIVE INGREDIENTS: AVOBENZONE 3 g/100 mL; OCTINOXATE 7.5 g/100 mL; OCTISALATE 5 g/100 mL; OXYBENZONE 6 g/100 mL
INACTIVE INGREDIENTS: WATER; C12-15 ALKYL BENZOATE; YEAST; AMINO ACIDS; POLYSORBATE 20; GLYCERIN; BUTYLOCTYL SALICYLATE; STEARIC ACID; GLYCERYL MONOSTEARATE; TRICALCIUM PHOSPHATE; CYCLOMETHICONE 5; CYCLOMETHICONE 6; SORBITAN MONOOLEATE; SHIITAKE MUSHROOM; CAMELLIA OLEIFERA LEAF; GREEN TEA LEAF; POMEGRANATE; CUCUMBER; ARNICA MONTANA FLOWER; ANACYCLUS PYRETHRUM ROOT; HYALURONATE SODIUM; ALPHA-TOCOPHEROL ACETATE; SODIUM ASCORBYL PHOSPHATE; TROLAMINE; EDETATE DISODIUM; PHENOXYETHANOL; METHYLPARABEN; ETHYLPARABEN; BUTYLPARABEN; PROPYLPARABEN; DIAZOLIDINYL UREA

PHOTO
DYNAMIC
therapy™

Drug Facts

ACTIVE INGREDIENT

Active Ingredient | Purpose
Avobenzone 3.0% | Sunscreen
Octinoxate 7.5% | Sunscreen
Octisalate 5.0% | Sunscreen
Oxybenzone 6.0% | Sunscreen

Use

Broad spectrum protection

Warnings

- For external use only.

WHEN USING

- UV exposure from the sun increases the risk of skin cancer, premature skin aging, and other skin damage. It is important to decrease UV exposure by limiting time in the sun, wearing protective clothing and using a sunscreen.
- Do not get into eyes. Rinse with water to remove.

- Stop use and consult a doctor if skin rash occurs.

- Keep out of reach of children.

Directions

Apply daily. Do not seek additional sun exposure. Contains broad spectrum SPF 30. For best results, apply generously 15 minutes prior to sun exposure. Reapply every 2 hours while outdoors. For children under 6 months of age: consult a doctor. Store at room temperature 59-86°F / 15-30°C.

Other Ingredients

Aqua (Water), C12-15 Alkyl Benzoate, Yeast Amino Acids, Polysorbate 20, Glycerin, Butyloctyl Salicylate, Methyl Methacrylate / Glycol Dimethacrylate Crosspolymer, Stearic Acid, Glyceryl Stearate SE, Tricalcium Phosphate, Cyclohexasiloxane, Cyclopentasiloxane, Sorbitan Oleate, Lentinula Edodes (Shiitake Mushroom) Extract, Benzylidene Dimethoxydimethylindanone, Morinda Citrifolia Extract, Camellia Oleifera (Green Tea) Leaf Extract, Camellia Sinensis (White Tea) Leaf Extract, Punica Granatum (Pomegranate) Fruit Extract, Cucumis Sativus (Cucumber) Fruit Extract, Arnica Montana Flower Extract, Anacyclus Pyrethrum Root Extract, Sodium Hyaluronate, Ubiquinone, Tocopherol, Tocopheryl Acetate, Sodium Ascorbyl Phosphate, Carbomer, Acrylates / C10-30 Alkyl Acrylate Crosspolymer, Triethanolamine, Disodium EDTA, Phenoxyethanol, Methylparaben, Ethylparaben, Butylparaben, Propylparaben

Questions or Comments?

ask@DERMAdoctor.com

www.DERMAdoctor.com®

PRINCIPAL DISPLAY PANEL - 30 ml Carton

PHOTO
DYNAMIC
therapy™

sunlight-activated
laser lotion with
spf 30

anti-aging

DERMAdoctor®

30 ml – 1 oz e